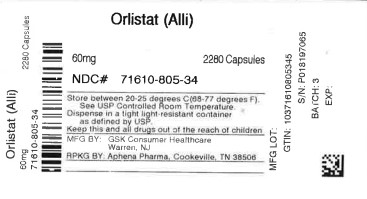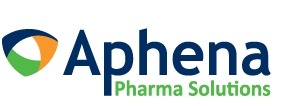 DRUG LABEL: ALLI
NDC: 71610-805 | Form: CAPSULE
Manufacturer: Aphena Pharma Solutions - Tennessee, LLC			
Category: otc | Type: HUMAN OTC DRUG LABEL
Date: 20240327

ACTIVE INGREDIENTS: ORLISTAT 60 mg/1 1
INACTIVE INGREDIENTS: FD&C BLUE NO. 2; GELATIN, UNSPECIFIED; FERROUS OXIDE; MICROCRYSTALLINE CELLULOSE; POVIDONE, UNSPECIFIED; SODIUM LAURYL SULFATE; SODIUM STARCH GLYCOLATE TYPE A; TALC; TITANIUM DIOXIDE

Drug Facts

Active ingredient (in each sealed capsule)

Orlistat 60 mg

Purpose

Weight loss aid

Use

- for weight loss in overweight adults, 18 years and older, when used along with a reduced-calorie and low-fat diet

Warnings

Organ transplant alert:

- do not use if you have had an organ transplant. Orlistat interferes with the medicines used to prevent transplant rejection.

Allergy alert:

- do not use if you are allergic to any of the ingredients in orlistat capsules

Do not use

- if you are taking cyclosporine
- if you have been diagnosed with problems absorbing food
- if you are not overweight

Ask a doctor before use if you have ever had

- gallbladder problems
- kidney stones
- pancreatitis

Ask a doctor or pharmacist before use if you are

- taking any of the following prescription medications. Some prescription doses may need to be adjusted, or some medications may not work as well when used with orlistat.
- anticoagulants (blood thinning medicine)
- amiodarone (heart medicine)
- diabetes medicine
- thyroid disease medicine
- seizure medicine
- antiretrovirals (HIV medicine)
- taking any other weight loss products

When using this product

- take a multivitamin once a day, at bedtime. Orlistat can reduce the absorption of some vitamins.
- follow a well-balanced, reduced-calorie, low-fat diet. Try starting this diet before taking orlistat.
- orlistat works by preventing the absorption of some of the fat you eat. The fat passes out of your body, so you may have bowel changes. You may get:
  - gas with oily spotting
  - loose stools
  - more frequent stools that may be hard to control
- eating a low-fat diet lowers the chance of having these bowel changes
- for every 5 pounds you lose from diet alone, orlistat can help you lose 2-3 pounds more. In studies, most people lost 5-10 pounds over 6 months.

Stop use and ask a doctor if

- you develop itching, yellow eyes or skin, dark urine or loss of appetite. There have been rare reports of liver injury in people taking orlistat.
- severe or continuous abdominal pain occurs. This may be a sign of a serious medical condition.
- you are taking medicine for seizures and your seizures happen more often or get worse

Keep out of reach of children.

In case of overdose, get medical help or contact a Poison Control Center right away.

Directions

- read the enclosed brochure for other important information
- diet and exercise are the starting points for any weight loss program. Try these first before adding orlistat. Check with your doctor before starting any exercise program.
- to see if orlistat capsules are right for you, find your height on the chart to the right. You may consider starting a weight loss program with orlistat if your weight is the same or more than the weight shown for your height.
- for overweight adults 18 years and older:
  - take 1 capsule with each meal containing fat
  - do not take more than 3 capsules daily
- use with a reduced-calorie, low-fat diet and exercise program until you reach your weight loss goal. Most weight loss occurs in the first 6 months.
- if you stop taking orlistat, continue with your diet and exercise program
- if you start to regain weight after you stop taking orlistat, you may need to start taking orlistat again along with your diet and exercise program
- take a multivitamin once a day, at bedtime, when using orlistat

Ht. / Wt.
4’10” | 129 lbs.
4’11” | 133 lbs.
5’0” | 138 lbs.
5’1” | 143 lbs.
5’2” | 147 lbs.
5’3” | 152 lbs.
5’4” | 157 lbs.
5’5” | 162 lbs.
5’6” | 167 lbs.
5’7” | 172 lbs.
5’8” | 177 lbs.
5’9” | 182 lbs.
5’10” | 188 lbs.
5’11” | 193 lbs.
6’0” | 199 lbs.
6’1” | 204 lbs.
6’2” | 210 lbs.
6’3” | 216 lbs.
6’4” | 221 lbs.
6’5” | 227 lbs.

Other information

- store at 20 - 25oC (68 - 77oF)
- protect drug from excessive light, humidity and temperatures over 30oC (86oF)

Inactive ingredients

FD&C Blue No. 2, edible ink, gelatin, iron oxide, microcrystalline cellulose, povidone, sodium lauryl sulfate, sodium starch glycolate, talc, titanium dioxide

Questions or comments?

call toll-free 1-800-671-2554

Additional information

The Starter Pack includes:

- Read Me First brochure
- Up to 20 day supply (60 capsules)

For more information, visit www.myalli.com

TAMPER- EVIDENT features for your protection. The package has a security seal on both ends of the carton printed with the GSK logo. The bottle of capsules has a foil seal under the cap imprinted with the words “sealed for your protection”. Each individual capsule is sealed with a dark blue band around the center of the capsule. DO NOT USE THIS PRODUCT IF ANY OF THESE TAMPER-EVIDENT FEATURES ARE MISSING, TORN OR BROKEN.

For more information and to learn more about alli, visit us at www.my alli.com.

- 1-800-671-2554

Distributed by:

Haleon,Warren, NJ 07059

Trademarks are owned by or licensed to the Haleon group of companies.

©2023 Haleon group of companies or its licensor.

Made in India

REPACKAGING INFORMATION

Please reference the HOW SUPPLIED section listed above for a description of drug product's characteristics. This drug product has been received by Aphena Pharma Solutions - Tennessee, LLC in a manufacturer or distributor packaged configuration and repackaged in full compliance with all applicable cGMP regulations. The package configurations available from Aphena are listed below:

60mg
NDC 71610-805-34, Bottles of 2280 Capsules

Store between 20°-25°C (68°-77°F). See USP Controlled Room Temperature. Dispense in a tight light-resistant container as defined by USP. Keep this and all drugs out of the reach of children.
Repackaged by:
Cookeville,TN 38506
20240327JK

PRINCIPAL DISPLAY PANEL - 60mg

NDC 71610-805 - Orlistat (Alli) 60mg Capsules - Rx Only